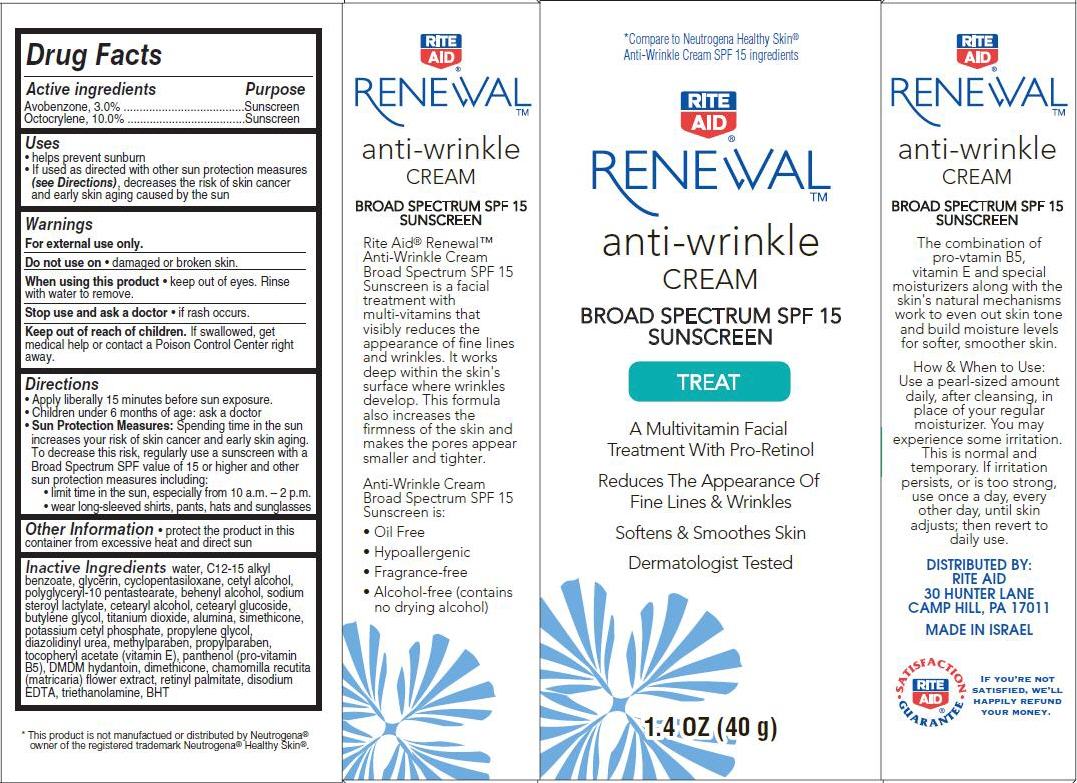 DRUG LABEL: Renewal Anti-Wrinkle
NDC: 11822-4591 | Form: CREAM
Manufacturer: Rite Aid Corporation
Category: otc | Type: HUMAN OTC DRUG LABEL
Date: 20140110

ACTIVE INGREDIENTS: AVOBENZONE 3 g/100 g; OCTOCRYLENE 10 g/100 g
INACTIVE INGREDIENTS: WATER; ALKYL (C12-15) BENZOATE; GLYCERIN; CYCLOMETHICONE 5; CETYL ALCOHOL; DOCOSANOL; SODIUM STEAROYL LACTYLATE; CETOSTEARYL ALCOHOL; CETEARYL GLUCOSIDE; BUTYLENE GLYCOL; TITANIUM DIOXIDE; ALUMINUM OXIDE; DIMETHICONE; POTASSIUM CETYL PHOSPHATE; PROPYLENE GLYCOL; DIAZOLIDINYL UREA; METHYLPARABEN; PROPYLPARABEN; .ALPHA.-TOCOPHEROL ACETATE; PANTHENOL; DMDM HYDANTOIN; CHAMOMILE; VITAMIN A PALMITATE; EDETATE DISODIUM; TROLAMINE; BUTYLATED HYDROXYTOLUENE

Renewal™ Anti-Wrinkle Cream

Active ingredient

Avobenzone 3.0%
Octocrylene 10.0%

Purpose

Sunscreen

Uses

- helps prevent sunburn
- If used as directed with other sun protection measures (see Directions), decreases the risk of skin cancer and early skin aging caused by the sun

Warnings

For external use only.

Do not use on

- damaged or broken skin.

When using this product

- keep out of eyes. Rinse with water to remove.

Stop use and ask a doctor

- if rash occurs.

Keep Out of Reach of Children.

If swallowed, get medical help or contact a Poison Control Center right away.

Directions

- Apply liberally 15 minutes before sun exposure.
- Children under 6 months of age: ask a doctor
- Sun Protection Measures: Spending time in the sun increases your risk of skin cancer and early skin aging. To decrease this risk, regularly use a sunscreen with a Broad Spectrum SPF value of 15 or higher and other sun protection measures including:
  - limit time in the sun, especially from 10 a.m. - 2 p.m.
  - wear long-sleeved shirts, pants, hats and sunglasses

Other Information

- protect the product in this container from excessive heat and direct sun

Inactive ingredients

water, C12-15 alkyl benzoate, glycerin, cyclopentasiloxane, cetyl alcohol, polyglyceryl-10 pentastearate, behenyl alcohol, sodium steroyl lactylate, cetearyl alcohol, cetearyl glucoside, butylene glycol, titanium dioxide, alumina, simethicone, potassium cetyl phosphate, propylene glycol, diazolidinyl urea, methylparaben, propyleparaben, tocopheryl acetate (vitamin E), panthenol (pro-vitamin B5), DMDM hydantoin, dimethicone, chamomilla recutita (matricaria) flower extract, retinyl palmitate, disodium EDTA, triethanolamine, BHT

Package/Label Principal Display Panel

Rite Aid® Renewal™
anti-wrinkle CREAM Broad Spectrum SPF 15 Sunscreen

TREAT

A Multivitamin Facial Treatment With Pro-Retinol
Reduces The Appearance Of Fine Lines & Wrinkles
Softens & Smoothes Skin
Dermatologist Tested

1.4 OZ (40 g)

*Compare to Neutrogena Healthy Skin® Anti-Wrinkle Cream SPF15 Ingredients

DISTRIBUTED BY:
RITE AID
30 HUNTER LANE
CAMP HILL, PA 17011
MADE IN ISRAEL

Carton Label